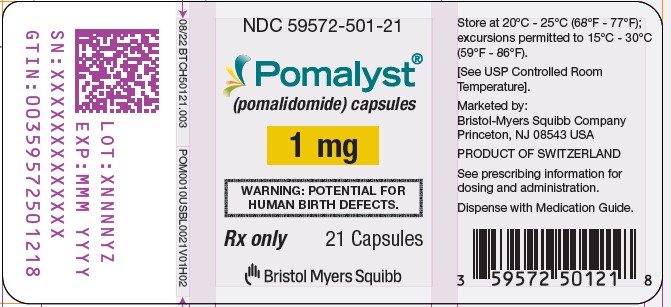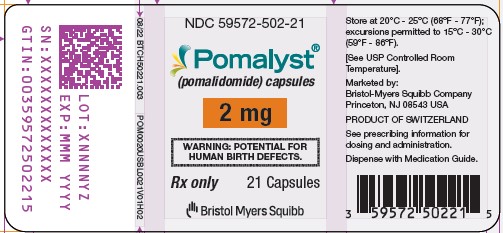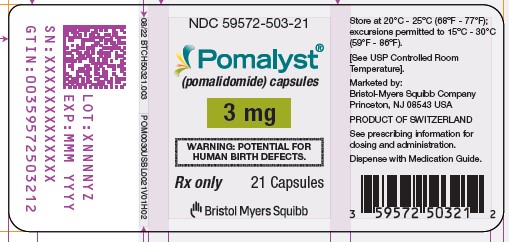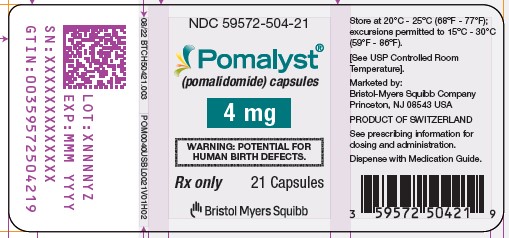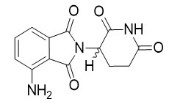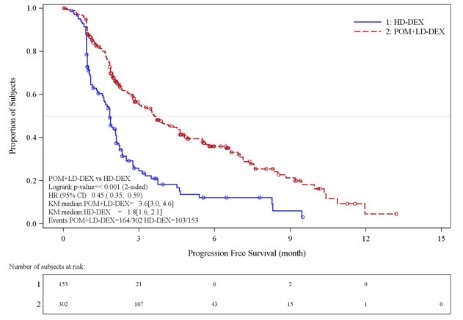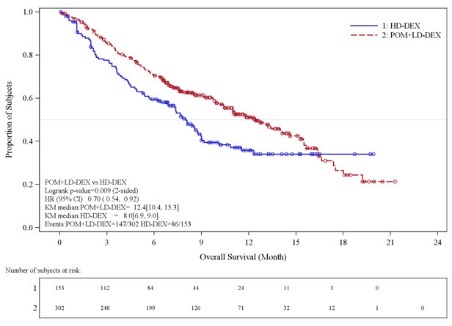 DRUG LABEL: Pomalyst
NDC: 59572-501 | Form: CAPSULE
Manufacturer: Celgene Corporation
Category: prescription | Type: HUMAN PRESCRIPTION DRUG LABEL
Date: 20250226

ACTIVE INGREDIENTS: POMALIDOMIDE 1 mg/1 1
INACTIVE INGREDIENTS: MANNITOL; STARCH, CORN; SODIUM STEARYL FUMARATE

HIGHLIGHTS OF PRESCRIBING INFORMATION

These highlights do not include all the information needed to use POMALYST safely and effectively. See full prescribing information for POMALYST.
POMALYST® (pomalidomide) capsules, for oral use
Initial U.S. Approval: 2013

RECENT MAJOR CHANGES

Boxed Warning | 2/2025
Warnings and Precautions (5.1, 5.2) | 2/2025

WARNING: EMBRYO-FETAL TOXICITY and VENOUS AND ARTERIAL THROMBOEMBOLISM

See full prescribing information for complete boxed warning

EMBRYO-FETAL TOXICITY

- POMALYST is contraindicated in pregnancy. POMALYST is a thalidomide analogue. Thalidomide is a known human teratogen that causes severe life-threatening birth defects (4, 5.1, 8.1).
- For females of reproductive potential: Exclude pregnancy before start of treatment. Prevent pregnancy during treatment by the use of 2 reliable methods of contraception (5.1, 8.3).

POMALYST is available only through a restricted program called PS-Pomalidomide REMS (5.2).

VENOUS AND ARTERIAL THROMBOEMBOLISM

- Deep venous thrombosis (DVT), pulmonary embolism (PE), myocardial infarction, and stroke occur in patients with multiple myeloma treated with POMALYST. Antithrombotic prophylaxis is recommended (5.3).

1 INDICATIONS AND USAGE

POMALYST is a thalidomide analogue indicated for the treatment of adult patients:

- in combination with dexamethasone, for patients with multiple myeloma (MM) who have received at least two prior therapies including lenalidomide and a proteasome inhibitor and have demonstrated disease progression on or within 60 days of completion of the last therapy (1.1).
- with AIDS-related Kaposi sarcoma (KS) after failure of highly active antiretroviral therapy (HAART) or in patients with KS who are HIV-negative. This indication is approved under accelerated approval based on overall response rate. Continued approval for this indication may be contingent upon verification and description of clinical benefit in a confirmatory trial(s) (1.2).

2 DOSAGE AND ADMINISTRATION

- MM: 4 mg per day taken orally on Days 1 through 21 of repeated 28-day cycles until disease progression (2.2). Refer to section 14.1 for dexamethasone dosing (14.1).
- KS: 5 mg per day taken orally on Days 1 through 21 of repeated 28-day cycles until disease progression or unacceptable toxicity (2.3).
- Modify the dosage for certain patients with renal impairment (2.7, 8.6) or hepatic impairment (2.8, 8.7).

3 DOSAGE FORMS AND STRENGTHS

Capsules: 1 mg, 2 mg, 3 mg, and 4 mg (3)

4 CONTRAINDICATIONS

- Pregnancy (4.1)
- Hypersensitivity (4.2)

5 WARNINGS AND PRECAUTIONS

- Increased Mortality: Observed in patients with MM when pembrolizumab was added to dexamethasone and a thalidomide analogue (5.4).
- Hematologic Toxicity: Neutropenia was the most frequently reported Grade 3/4 adverse event. Monitor patients for hematologic toxicities, especially neutropenia (5.5).
- Hepatotoxicity: Hepatic failure including fatalities; monitor liver function tests monthly (5.6).
- Severe Cutaneous Reactions: Discontinue POMALYST for severe reactions (5.7).
- Tumor Lysis Syndrome (TLS): Monitor patients at risk of TLS (i.e., those with high tumor burden) and take appropriate precautions (5.11).
- Hypersensitivity: Monitor patients for potential hypersensitivity. Discontinue POMALYST for angioedema and anaphylaxis (5.12).

6 ADVERSE REACTIONS

- MM: Most common adverse reactions (≥30%) included fatigue and asthenia, neutropenia, anemia, constipation, nausea, diarrhea, dyspnea, upper-respiratory tract infections, back pain, and pyrexia (6.1).
- KS: Most common adverse reactions including laboratory abnormalities (≥30%) are decreased absolute neutrophil count or white blood cells, elevated creatinine or glucose, rash, constipation, fatigue, decreased hemoglobin, platelets, phosphate, albumin, or calcium, increased ALT, nausea, and diarrhea (6.1).

To report SUSPECTED ADVERSE REACTIONS, contact Bristol Myers Squibb at 1-800-721-5072 or FDA at 1-800-FDA-1088 or www.fda.gov/medwatch.

7 DRUG INTERACTIONS

Strong CYP1A2 Inhibitors: Avoid concomitant use of strong CYP1A2 inhibitors. If concomitant use of a strong CYP1A2 inhibitor is unavoidable, reduce POMALYST dose to 2 mg (2.6, 7.1, 12.3).

8 USE IN SPECIFIC POPULATIONS

- Lactation: Advise women not to breastfeed (8.2).

FULL PRESCRIBING INFORMATION

WARNING: EMBRYO-FETAL TOXICITY and VENOUS AND ARTERIAL THROMBOEMBOLISM

Embryo-Fetal Toxicity

- POMALYST is contraindicated in pregnancy. POMALYST is a thalidomide analogue. Thalidomide is a known human teratogen that causes severe birth defects or embryo-fetal death. In females of reproductive potential, obtain 2 negative pregnancy tests before starting POMALYST treatment.
- Females of reproductive potential must use 2 forms of contraception or continuously abstain from heterosexual sex during and for 4 weeks after stopping POMALYST treatment [see Contraindications (4), Warnings and Precautions (5.1) and Use in Specific Populations (8.1, 8.3)].

POMALYST is only available through a restricted distribution program called PS-Pomalidomide REMS [see Warnings and Precautions (5.2)]. Information about PS-Pomalidomide REMS is available at www.PS-PomalidomideREMS.com or by calling the REMS Call Center at 1-888-423-5436.

Venous and Arterial Thromboembolism

- Deep venous thrombosis (DVT), pulmonary embolism (PE), myocardial infarction, and stroke occur in patients with multiple myeloma treated with POMALYST. Prophylactic antithrombotic measures were employed in clinical trials. Thromboprophylaxis is recommended, and the choice of regimen should be based on assessment of the patient's underlying risk factors [see Warnings and Precautions (5.3)].

1 INDICATIONS AND USAGE

1.1 Multiple Myeloma

POMALYST, in combination with dexamethasone, is indicated for adult patients with multiple myeloma (MM) who have received at least two prior therapies including lenalidomide and a proteasome inhibitor and have demonstrated disease progression on or within 60 days of completion of the last therapy.

1.2 Kaposi Sarcoma

POMALYST is indicated for the treatment of:

- Adult patients with AIDS-related Kaposi sarcoma (KS) after failure of highly active antiretroviral therapy (HAART).
- Kaposi sarcoma (KS) in adult patients who are HIV-negative.

This indication is approved under accelerated approval based on overall response rate [see Clinical Studies (14.2)]. Continued approval for this indication may be contingent upon verification and description of clinical benefit in a confirmatory trial(s).

2 DOSAGE AND ADMINISTRATION

2.1 Pregnancy Testing Prior to Administration

Females of reproductive potential must have negative pregnancy testing and use contraception methods before initiating POMALYST [see Warnings and Precautions (5.1) and Use in Specific Populations (8.1, 8.3)].

2.2 Recommended Dosage for Multiple Myeloma

The recommended dosage of POMALYST is 4 mg once daily orally with or without food on Days 1 through 21 of each 28-day cycle until disease progression. Give POMALYST in combination with dexamethasone [see Clinical Studies (14.1)].

2.3 Recommended Dosage for Kaposi Sarcoma

The recommended dosage of POMALYST is 5 mg once daily taken orally with or without food on Days 1 through 21 of each 28-day cycle until disease progression or unacceptable toxicity. Continue HAART as HIV treatment in patients with AIDS-related Kaposi sarcoma (KS) [see Clinical Studies (14.2)].

2.4 Dosage Modifications for Hematologic Adverse Reactions

Multiple Myeloma: Dosage Modifications for Hematologic Adverse Reactions

Initiate a new cycle of POMALYST in patients with multiple myeloma (MM) when the neutrophil count is at least 500 per mcL and the platelet count is at least 50,000 per mcL.

Dosage modification for POMALYST for hematologic adverse reactions in patients with MM are summarized in Table 1.

Table 1: Dosage Modifications for POMALYST for Hematologic in MM
Adverse Reaction | Severity | Dosage Modification
Neutropenia [see Warnings and Precautions (5.5)] | - ANC less than 500 per mcL or febrile neutropenia (fever greater than or equal to 38.5°C and ANC less than 1,000 per mcL) | - Withhold POMALYST until ANC is greater than or equal to 500 per mcL; follow CBC weekly. - Resume POMALYST dose at 1 mg less than the previous dose.*
Neutropenia [see Warnings and Precautions (5.5)] | - For each subsequent drop of ANC less than 500 per mcL | - Withhold POMALYST until ANC is greater than or equal to 500 mcL. - Resume POMALYST dose at 1 mg less than the previous dose.*
Thrombocytopenia [see Warnings and Precautions (5.5)] | - Platelets less than 25,000 per mcL | - Withhold POMALYST until platelets are greater than or equal to 50,000 per mcL; follow CBC weekly. - Resume POMALYST dose at 1 mg less than the previous dose*
Thrombocytopenia [see Warnings and Precautions (5.5)] | - For each subsequent drop of platelets less than 25,000 per mcL | - Withhold POMALYST until platelets are greater than or equal to 50,000 per mcL. - Resume POMALYST at 1 mg less than the previous dose*
* Permanently discontinue POMALYST if unable to tolerate 1 mg once daily.
ANC= absolute neutrophil count

Kaposi Sarcoma: Dosage Modifications for Hematologic Adverse Reactions

Initiate a new cycle of POMALYST in patients with KS when the neutrophil count is at least 1000 per mcL and the platelet count is at least 75,000 per mcL.

Dose modifications for POMALYST for hematologic adverse reactions in patients with KS are summarized in Table 2.

Table 2: Dosage Modifications for POMALYST for Hematologic Adverse Reactions in KS
Adverse Reaction | Severity | Dosage Modification
Neutropenia [see Warnings and Precautions (5.5)] | ANC 500 to less than 1,000 per mcL | Day 1 of cycle; - Withhold POMALYST until ANC is greater than or equal to 1,000 per mcL. - Resume POMALYST at the same dose.; During cycle; - Continue POMALYST at the current dose.
Neutropenia [see Warnings and Precautions (5.5)] | ANC less than 500 per mcL | - Withhold POMALYST until ANC is greater than or equal to 1,000 per mcL. - Resume POMALYST at the same dose.
Febrile Neutropenia [see Warnings and Precautions (5.5)] | ANC less than 1,000 per mcL and single temperature greater than or equal to 38.3°C or ANC less than 1,000 per mcL and sustained temperature greater than or equal to 38°C for more than 1 hour | - Withhold POMALYST until ANC is greater than or equal to 1,000 per mcL. - Resume POMALYST at dose 1 mg less than the previous dose.*
Thrombocytopenia [see Warnings and Precautions (5.5)] | Platelet count 25,000 to less than 50,000 per mcL | Day 1 of cycle; - Withhold POMALYST until platelet count is greater than or equal to 50,000 per mcL. - Resume POMALYST at the same dose.; During cycle:; - Continue POMALYST at the current dose.
Thrombocytopenia [see Warnings and Precautions (5.5)] | Platelet count less than 25,000 per mcL | Permanently discontinue POMALYST.
* Permanently discontinue POMALYST if unable to tolerate 1mg once daily.
ANC= absolute neutrophil count

2.5 Dosage Modifications for Non-Hematologic Adverse Reactions

Permanently discontinue POMALYST for angioedema, anaphylaxis, Grade 4 rash, skin exfoliation, bullae, or any other severe dermatologic reaction [See Warnings and Precautions (5.7, 5.12)].

For other Grade 3 or 4 toxicities, hold treatment and restart treatment at 1 mg less than the previous dose when toxicity has resolved to less than or equal to Grade 2 at the physician's discretion.

2.6 Dosage Modifications for Strong CYP1A2 Inhibitors

Avoid concomitant use of POMALYST with strong CYP1A2 inhibitors. If concomitant use of a strong CYP1A2 inhibitor is unavoidable, reduce POMALYST dose to 2 mg [see Drug Interactions (7.1) and Clinical Pharmacology (12.3)].

2.7 Dosage Modification for Severe Renal Impairment on Hemodialysis

Take POMALYST after completion of dialysis procedure on hemodialysis days [see Use in Specific Populations (8.6) and Clinical Pharmacology (12.3)].

- For patients with MM with severe renal impairment requiring dialysis, reduce the recommended dosage to 3 mg orally daily.
- For patients with KS with severe renal impairment requiring dialysis, reduce the recommended dosage to 4 mg orally daily.

2.8 Dosage Modification for Hepatic Impairment

Multiple Myeloma

For patients with MM with mild or moderate hepatic impairment (Child-Pugh A or B), reduce the recommended dosage to 3 mg orally daily.

For patients with MM with severe hepatic impairment (Child-Pugh C), reduce the recommended dosage to 2 mg [see Use in Specific Populations (8.7) and Clinical Pharmacology (12.3)].

Kaposi Sarcoma

For patients with KS with mild, moderate, or severe hepatic impairment (Child-Pugh A, B, or C), reduce the recommended dosage to 3 mg orally daily [see Use in Specific Populations (8.7) and Clinical Pharmacology (12.3)].

2.9 Administration

Swallow capsules whole with water. Do not break, chew, or open the capsules.

POMALYST may be taken with or without food.

3 DOSAGE FORMS AND STRENGTHS

- Capsules:1 mg, dark blue opaque cap and yellow opaque body, imprinted "POML" on the cap in white ink and "1 mg" on the body in black ink
- 2 mg, dark blue opaque cap and orange opaque body, imprinted "POML" on the cap and "2 mg" on the body in white ink
- 3 mg, dark blue opaque cap and green opaque body, imprinted "POML" on the cap and "3 mg" on the body in white ink
- 4 mg, dark blue opaque cap and blue opaque body, imprinted "POML" on the cap and "4 mg" on the body in white ink

4 CONTRAINDICATIONS

4.1 Pregnancy

POMALYST is contraindicated in females who are pregnant. POMALYST can cause fetal harm when administered to a pregnant female [see Warnings and Precautions (5.1) and Use in Specific Populations (8.1)]. Pomalidomide is a thalidomide analogue and is teratogenic in both rats and rabbits when administered during the period of organogenesis. If the patient becomes pregnant while taking this drug, the patient should be apprised of the potential risk to a fetus.

4.2 Hypersensitivity

POMALYST is contraindicated in patients who have demonstrated severe hypersensitivity (e.g., angioedema, anaphylaxis) to pomalidomide or any of the excipients [see Warnings and Precautions (5.7), Description (11)].

5 WARNINGS AND PRECAUTIONS

5.1 Embryo-Fetal Toxicity

POMALYST is a thalidomide analogue and is contraindicated for use during pregnancy. Thalidomide is a known human teratogen that causes severe birth defects or embryo-fetal death [see Use in Specific Populations (8.1)]. POMALYST is only available through PS-Pomalidomide REMS [see Warnings and Precautions (5.2)].

Females of Reproductive Potential

Females of reproductive potential must avoid pregnancy for at least 4 weeks before beginning POMALYST therapy, during therapy, during dose interruptions and for at least 4 weeks after completing therapy.

Females must commit either to abstain continuously from heterosexual sexual intercourse or to use 2 methods of reliable birth control, beginning 4 weeks prior to initiating treatment with POMALYST, during therapy, during dose interruptions, and continuing for 4 weeks following discontinuation of POMALYST therapy.

Two negative pregnancy tests must be obtained prior to initiating therapy. The first test should be performed within 10-14 days and the second test within 24 hours prior to prescribing POMALYST therapy and then weekly during the first month, then monthly thereafter in females with regular menstrual cycles, or every 2 weeks in females with irregular menstrual cycles [see Use in Specific Populations (8.3)].

Males

Pomalidomide is present in the semen of patients receiving the drug. Therefore, males must always use a latex or synthetic condom during any sexual contact with females of reproductive potential while taking POMALYST and for up to 4 weeks after discontinuing POMALYST, even if they have undergone a successful vasectomy. Male patients taking POMALYST must not donate sperm [see Use in Specific Populations (8.3)].

Blood Donation

Patients must not donate blood during treatment with POMALYST and for 4 weeks following discontinuation of the drug because the blood might be given to a pregnant female patient whose fetus must not be exposed to POMALYST.

5.2 PS-Pomalidomide REMS

Because of the embryo-fetal risk [see Warnings and Precautions (5.1)], POMALYST is available only through a restricted program under a Risk Evaluation and Mitigation Strategy (REMS), "PS-Pomalidomide REMS".

Required components of PS-Pomalidomide REMS include the following:

- Prescribers must be certified with PS-Pomalidomide REMS by enrolling and complying with the REMS requirements.
- Patients must sign a Patient-Physician Agreement Form and comply with the REMS requirements. In particular, female patients of reproductive potential who are not pregnant must comply with the pregnancy testing and contraception requirements [see Use in Specific Populations (8.3)] and males must comply with contraception requirements [see Use in Specific Populations (8.3)].
- Pharmacies must be certified with PS-Pomalidomide REMS, must only dispense to patients who are authorized to receive POMALYST and comply with REMS requirements.

Further information about PS-Pomalidomide REMS is available at www.PS-PomalidomideREMS.com or by telephone at 1-888-423-5436.

5.3 Venous and Arterial Thromboembolism

Venous thromboembolic events (deep venous thrombosis and pulmonary embolism) and arterial thromboembolic events (myocardial infarction and stroke) have been observed in patients treated with POMALYST. In Trial 2, where anticoagulant therapies were mandated, thromboembolic events occurred in 8.0% of patients treated with POMALYST and low dose-dexamethasone (Low-dose Dex), and 3.3% of patients treated with high-dose dexamethasone. Venous thromboembolic events (VTE) occurred in 4.7% of patients treated with POMALYST and Low-dose Dex, and 1.3% of patients treated with high-dose dexamethasone. Arterial thromboembolic events include terms for arterial thromboembolic events, ischemic cerebrovascular conditions, and ischemic heart disease. Arterial thromboembolic events occurred in 3.0% of patients treated with POMALYST and Low-dose Dex, and 1.3% of patients treated with high-dose dexamethasone.

Patients with known risk factors, including prior thrombosis, may be at greater risk, and actions should be taken to try to minimize all modifiable factors (e.g., hyperlipidemia, hypertension, smoking). Thromboprophylaxis is recommended, and the choice of regimen should be based on assessment of the patient's underlying risk factors.

5.4 Increased Mortality in Patients with Multiple Myeloma When Pembrolizumab Is Added to a Thalidomide Analogue and Dexamethasone

In two randomized clinical trials in patients with MM, the addition of pembrolizumab to a thalidomide analogue plus dexamethasone, a use for which no PD-1 or PD-L1 blocking antibody is indicated, resulted in increased mortality. Treatment of patients with MM with a PD-1 or PD-L1 blocking antibody in combination with a thalidomide analogue plus dexamethasone is not recommended outside of controlled clinical trials.

5.5 Hematologic Toxicity

Multiple Myeloma

In trials 1 and 2 in patients who received POMALYST + Low-dose Dex, neutropenia was the most frequently reported Grade 3 or 4 adverse reaction, followed by anemia and thrombocytopenia. Neutropenia of any grade was reported in 51% of patients in both trials. The rate of Grade 3 or 4 neutropenia was 46%. The rate of febrile neutropenia was 8%.

Monitor patients for hematologic toxicities, especially neutropenia. Monitor complete blood counts weekly for the first 8 weeks and monthly thereafter. Patients may require dose interruption and/or modification [see Dosage and Administration (2.4)].

Kaposi Sarcoma

In Trial 12-C-0047, hematologic toxicities were the most common (all grades and Grade 3 or 4) adverse reactions [see Adverse Reactions (6.1)]. Fifty percent of patients had Grade 3 or 4 neutropenia. Monitor patients for hematologic toxicities, especially decreased neutrophils. Monitor complete blood counts every 2 weeks for the first 12 weeks and monthly thereafter. Withhold, reduce the dose, or permanently discontinue POMALYST based on the severity of the reaction [see Dosage and Administration (2.4)].

5.6 Hepatotoxicity

Hepatic failure, including fatal cases, has occurred in patients treated with POMALYST. Elevated levels of alanine aminotransferase and bilirubin have also been observed in patients treated with POMALYST. Monitor liver function tests monthly. Stop POMALYST upon elevation of liver enzymes and evaluate. After return to baseline values, treatment at a lower dose may be considered.

5.7 Severe Cutaneous Reactions

Severe cutaneous reactions including Stevens-Johnson syndrome (SJS), toxic epidermal necrolysis (TEN), and drug reaction with eosinophilia and systemic symptoms (DRESS) have been reported. DRESS may present with a cutaneous reaction (such as rash or exfoliative dermatitis), eosinophilia, fever, and/or lymphadenopathy with systemic complications such as hepatitis, nephritis, pneumonitis, myocarditis, and/or pericarditis. These reactions can be fatal. Consider POMALYST interruption or discontinuation for Grade 2 or 3 skin rash. Permanently discontinue POMALYST for Grade 4 rash, exfoliative or bullous rash, or for other severe cutaneous reactions such as SJS, TEN or DRESS [see Dosage and Administration (2.5)].

5.8 Dizziness and Confusional State

In trials 1 and 2 in patients who received POMALYST + Low-dose Dex, 14% of patients experienced dizziness and 7% of patients experienced a confusional state; 1% of patients experienced Grade 3 or 4 dizziness, and 3% of patients experienced Grade 3 or 4 confusional state. Instruct patients to avoid situations where dizziness or confusional state may be a problem and not to take other medications that may cause dizziness or confusional state without adequate medical advice.

5.9 Neuropathy

In trials 1 and 2 in patients who received POMALYST + Low-dose Dex, 18% of patients experienced neuropathy, with approximately 12% of the patients experiencing peripheral neuropathy. Two percent of patients experienced Grade 3 neuropathy in trial 2. There were no cases of Grade 4 neuropathy adverse reactions reported in either trial.

5.10 Risk of Second Primary Malignancies

Cases of acute myelogenous leukemia have been reported in patients receiving POMALYST as an investigational therapy outside of MM.

5.11 Tumor Lysis Syndrome

Tumor lysis syndrome (TLS) may occur in patients treated with POMALYST. Patients at risk for TLS are those with high tumor burden prior to treatment. These patients should be monitored closely and appropriate precautions taken.

5.12 Hypersensitivity

Hypersensitivity, including angioedema, anaphylaxis, and anaphylactic reactions to POMALYST have been reported. Permanently discontinue POMALYST for angioedema or anaphylaxis [see Dosage and Administration (2.5)].

6 ADVERSE REACTIONS

The following clinically significant adverse reactions are described in detail in other labeling sections:

- Embryo-Fetal Toxicity [see Warnings and Precautions (5.1, 5.2)]
- Venous and Arterial Thromboembolism [see Warnings and Precautions (5.3)]
- Increased Mortality in Patients with Multiple Myeloma When Pembrolizumab Is Added to a Thalidomide Analogue and Dexamethasone [see Warnings and Precautions (5.4)]
- Hematologic Toxicity [see Warnings and Precautions (5.5)]
- Hepatotoxicity [see Warnings and Precautions (5.6)]
- Severe Cutaneous Reactions [see Warnings and Precautions (5.7)]
- Dizziness and Confusional State [see Warnings and Precautions (5.8)]
- Neuropathy [see Warnings and Precautions (5.9)]
- Risk of Second Primary Malignancies [see Warnings and Precautions (5.10)]
- Tumor Lysis Syndrome [see Warnings and Precautions (5.11)]
- Hypersensitivity [see Warnings and Precautions (5.12)]

6.1 Clinical Trials Experience

Because clinical trials are conducted under widely varying conditions, adverse reaction rates observed in the clinical trials of a drug cannot be directly compared to rates in the clinical trials of another drug and may not reflect the rates observed in practice.

Multiple Myeloma (MM)

In Trial 1, data were evaluated from 219 patients (safety population) who received treatment with POMALYST + Low-dose Dex (112 patients) or POMALYST alone (107 patients). Median number of treatment cycles was 5. Sixty-seven percent of patients in the study had a dose interruption of either drug due to adverse reactions. Forty-two percent of patients in the study had a dose reduction of either drug due to adverse reactions. The discontinuation rate due to adverse reactions was 11%.

In Trial 2, data were evaluated from 450 patients (safety population) who received treatment with POMALYST + Low-dose Dex (300 patients) or High-dose Dexamethasone (High-dose Dex) (150 patients). The median number of treatment cycles for the POMALYST + Low-dose Dex arm was 5. In the POMALYST + Low-dose Dex arm, 67% of patients had a dose interruption of POMALYST, the median time to the first dose interruption of POMALYST was 4.1 weeks. Twenty-seven percent of patients had a dose reduction of POMALYST, the median time to the first dose reduction of POMALYST was 4.5 weeks. Eight percent of patients discontinued POMALYST due to adverse reactions.

Tables 3 and 4 summarize the adverse reactions reported in Trials 1 and 2, respectively.

Table 3: Adverse Reactions in Any POMALYST Treatment Arm in Trial 1*
 | All Adverse Reactions ≥10% in Either Arm |  | Grade 3 or 4 ≥5% in Either Arm
Body System Adverse Reaction | POMALYSTa (N=107) | POMALYST + Low-dose Dex (N=112) | POMALYST (N=107) | POMALYST + Low-dose Dex (N=112)
Number (%) of patients with at least one adverse reaction | 107 (100) | 112 (100) | 98 (92) | 102 (91)
Blood and lymphatic system disorders
Neutropenia b | 57 (53) | 55 (49) | 51 (48) | 46 (41)
Anemia b | 41 (38) | 47 (42) | 25 (23) | 24 (21)
Thrombocytopenia b | 28 (26) | 26 (23) | 24 (22) | 21 (19)
Leukopenia | 14 (13) | 22 (20) | 7 (7) | 11 (10)
Febrile neutropenia b | <10% | <10% | 6 (6) | 3 (3)
Lymphopenia | 4 (4) | 17 (15) | 2 (2) | 8 (7)
General disorders and administration site conditions
Fatigue and asthenia b | 62 (58) | 70 (63) | 13 (12) | 19 (17)
Edema peripheral | 27 (25) | 19 (17) | 0 (0.0) | 0 (0.0)
Pyrexia b | 25 (23) | 36 (32) | <5% | <5%
Chills | 11 (10) | 14 (13) | 0 (0.0) | 0 (0.0)
Gastrointestinal disorders
Nausea b | 39 (36) | 27 (24) | <5% | <5%
Constipation b | 38 (36) | 41 (37) | <5% | <5%
Diarrhea | 37 (35) | 40 (36) | <5% | <5%
Vomiting b | 15 (14) | 16 (14) | <5% | 0 (0.0)
Musculoskeletal and connective tissue disorders
Back pain b | 37 (35) | 36 (32) | 15 (14) | 11 (10)
Musculoskeletal chest pain | 25 (23) | 22 (20) | <5% | 0 (0.0)
Muscle spasms | 23 (21) | 22 (20) | <5% | <5%
Arthralgia | 18 (17) | 17 (15) | <5% | <5%
Muscular weakness | 15 (14) | 15 (13) | 6 (6) | 4 (4)
Bone pain | 13 (12) | 8 (7) | <5% | <5%
Musculoskeletal pain | 13 (12) | 19 (17) | <5% | <5%
Pain in extremity | 8 (7) | 16 (14) | 0 (0.0) | <5%
Infections and infestations
Upper respiratory tract infection | 40 (37) | 32 (29) | <5% | <5%
Pneumonia b | 30 (28) | 38 (34) | 21 (20) | 32 (29)
Urinary tract infection b | 11 (10) | 19 (17) | 2 (2) | 10 (9)
Sepsis b | <10% | <10% | 6 (6) | 5 (4)
Metabolism and nutrition disorders
Decreased appetite | 25 (23) | 21 (19) | <5% | 0 (0.0)
Hypercalcemia b | 23 (21) | 13 (12) | 11 (10) | 1 (<1)
Hypokalemia | 13 (12) | 13 (12) | <5% | <5%
Hyperglycemia | 12 (11) | 17 (15) | <5% | <5%
Hyponatremia | 12 (11) | 14 (13) | <5% | <5%
Dehydration b | <10% | <10% | 5 (4.7) | 6 (5.4)
Hypocalcemia | 6 (6) | 13 (12) | 0 (0.0) | <5%
Respiratory, thoracic and mediastinal disorders
Dyspnea b | 38 (36) | 50 (45) | 8 (7) | 14 (13)
Cough | 18 (17) | 25 (22) | 0 (0.0) | 0 (0.0)
Epistaxis | 18 (17) | 12 (11) | <5% | 0 (0.0)
Productive cough | 10 (9) | 14 (13) | 0 (0.0) | 0 (0.0)
Oropharyngeal pain | 6 (6) | 12 (11) | 0 (0.0) | 0 (0.0)
Nervous system disorders
Dizziness | 24 (22) | 20 (18) | <5% | <5%
Peripheral neuropathy | 23 (21) | 20 (18) | 0 (0.0) | 0 (0.0)
Headache | 16 (15) | 15 (13) | 0 (0.0) | <5%
Tremor | 11 (10) | 15 (13) | 0 (0.0) | 0 (0.0)
Skin and subcutaneous tissue disorders
Rash | 22 (21) | 18 (16) | 0 (0.0) | <5%
Pruritus | 16 (15) | 10 (9) | 0 (0.0) | 0 (0.0)
Dry skin | 10 (9) | 12 (11) | 0 (0.0) | 0 (0.0)
Hyperhidrosis | 8 (7) | 18 (16) | 0 (0.0) | 0 (0.0)
Night sweats | 5 (5) | 14 (13) | 0 (0.0) | 0 (0.0)
Investigations
Blood creatinine increased b | 20 (19) | 11 (10) | 6 (6) | 3 (3)
Weight decreased | 16 (15) | 10 (9) | 0 (0.0) | 0 (0.0)
Weight increased | 1 (<1) | 12 (11) | 0 (0.0) | 0 (0.0)
Psychiatric disorders
Anxiety | 14 (13) | 8 (7) | 0 (0.0) | 0 (0.0)
Confusional state b | 13 (12) | 15 (13) | 6 (6) | 3 (3)
Insomnia | 7 (7) | 18 (16) | 0 (0.0) | 0 (0.0)
Renal and urinary disorders
Renal failure b | 16 (15) | 11 (10) | 9 (8) | 8 (7)
* Regardless of attribution of relatedness to POMALYST.
a POMALYST alone arm includes all patients randomized to the POMALYST alone arm who took study drug; 61 of the 107 patients had dexamethasone added during the treatment period.
b Serious adverse reactions were reported in at least 2 patients in any POMALYST treatment arm.
Data cutoff: 01 March 2013

Table 4: Adverse Reactions in Trial 2
 | All Adverse Reactions (≥5% in POMALYST + Low-dose Dex arm, and at least 2% higher than the High-dose-Dex arm) |  | Grade 3 or 4 (≥1% in POMALYST + Low-dose Dex arm, and at least 1% higher than the High-dose-Dex arm)
Body System Adverse Reaction | POMALYST + Low-dose Dex (N=300) | High-dose Dex (N=150) | POMALYST + Low-dose Dex (N=300) | High-dose Dex (N=150)
Number (%) of patients with at least one adverse reaction | 297 (99) | 149 (99) | 259 (86) | 127 (85)
Blood and lymphatic system disorders
Neutropenia b | 154 (51) | 31 (21) | 145 (48) | 24 (16)
Thrombocytopenia | 89 (30) a | 44 (29) a | 66 (22) a | 39 (26) a
Leukopenia | 38 (13) | 8 (5) | 27 (9) | 5 (3)
Febrile neutropenia b | 28 (9) | 0 (0.0) | 28 (9) | 0 (0.0)
General disorders and administration site conditions
Fatigue and asthenia | 140 (47) | 64 (43) | 26 (9) a | 18 (12) a
Pyrexia b | 80 (27) | 35 (23) | 9 (3) a | 7 (5) a
Edema peripheral | 52 (17) | 17 (11) | 4 (1) a | 3 (2) a
Pain | 11 (4) a | 3 (2) a | 5 (2) | 1 (<1)
Infections and infestations
Upper respiratory tract infection b | 93 (31) | 19 (13) | 9 (3) | 1 (<1)
Pneumonia b | 58 (19) | 20 (13) | 47 (16) | 15 (10)
Neutropenic sepsis b | 3 (1) a | 0 (0.0) a | 3 (1) | 0 (0.0)
Gastrointestinal disorders
Diarrhea | 66 (22) | 28 (19) | 3 (1) a | 2 (1) a
Constipation | 65 (22) | 22 (15) | 7 (2) | 0 (0.0)
Nausea | 45 (15) | 17 (11) | 3 (1) a | 2 (1) a
Vomiting | 23 (8) | 6 (4) | 3 (1) | 0 (0.0)
Musculoskeletal and connective tissue disorders
Back pain b | 59 (20) | 24 (16) | 15 (5) | 6 (4)
Bone pain b | 54 (18) | 21 (14) | 22 (7) | 7 (5)
Muscle spasms | 46 (15) | 11 (7) | 1 (<1) a | 1 (<1) a
Arthralgia | 26 (9) | 7 (5) | 2 (<1) a | 1 (<1) a
Pain in extremity | 20 (7) a | 9 (6) a | 6 (2) | 0 (0.0)
Respiratory, thoracic and mediastinal disorders
Dyspnea b | 76 (25) | 25 (17) | 17 (6) | 7 (5)
Cough | 60 (20) | 15 (10) | 2 (<1) a | 1 (<1) a
Chronic obstructive pulmonary disease b | 5 (2) a | 0 (0.0) a | 4 (1) | 0 (0.0)
Nervous system disorders
Peripheral neuropathy | 52 (17) | 18 (12) | 5 (2) a | 2 (1) a
Dizziness | 37 (12) | 14 (9) | 4 (1) a | 2 (1) a
Headache | 23 (8) | 8 (5) | 1 (<1) a | 0 (0.0) a
Tremor | 17 (6) | 2 (1) | 2 (<1) a | 0 (0.0) a
Depressed level of consciousness | 5 (2) a | 0 (0.0) a | 3 (1) | 0 (0.0)
Metabolism and nutrition disorders
Decreased appetite | 38 (13) | 12 (8) | 3 (1) a | 2 (1) a
Hypokalemia | 28 (9) a | 12 (8) a | 12 (4) | 4 (3)
Hypocalcemia | 12 (4) a | 9 (6) a | 5 (2) | 1 (<1)
Skin and subcutaneous tissue disorders
Rash | 23 (8) | 2 (1) | 3 (1) | 0 (0.0)
Pruritus | 22 (7) | 5 (3) | 0 (0.0) a | 0 (0.0) a
Hyperhidrosis | 15 (5) | 1 (<1) | 0 (0.0) a | 0 (0.0) a
Investigations
Neutrophil count decreased | 15 (5) | 1 (<1) | 14 (5) | 1 (<1)
Platelet count decreased | 10 (3) a | 3 (2) a | 8 (3) | 2 (1)
White blood cell count decreased | 8 (3) a | 1 (<1) a | 8 (3) | 0 (0.0)
Alanine aminotransferase increased | 7 (2) a | 2 (1) a | 5 (2) | 0 (0.0)
Aspartate aminotransferase increased | 4 (1) a | 2 (1) a | 3 (1) | 0 (0.0)
Lymphocyte count decreased | 3 (1) a | 1 (<1) a | 3 (1) | 0 (0.0)
Renal and urinary disorders
Renal failure | 31 (10) a | 18 (12) a | 19 (6) | 8 (5)
Injury, poisoning and procedural complications
Femur fracture b | 5 (2) a | 1 (<1) a | 5 (2) | 1 (<1)
Reproductive system and breast disorders
Pelvic pain | 6 (2) a | 3 (2) a | 4 (1) | 0 (0.0)
a Percentage did not meet the criteria to be considered as an adverse reaction for POMALYST for that category of event (i.e., all adverse events or Grade 3 or 4 adverse events).
b Serious adverse reactions were reported in at least 3 patients in the POM + Low-dose Dex arm, AND at least 1% higher than the High-dose-Dex arm percentage.
Data cutoff: 01 March 2013

Other Adverse Reactions

Other adverse reactions of POMALYST in patients with MM, not described above, and considered important:

Cardiac Disorders: Myocardial infarction, Atrial fibrillation, Angina pectoris, Cardiac failure congestive

Ear and Labyrinth Disorders: Vertigo

Gastrointestinal disorders: Abdominal pain

General Disorders and Administration Site Conditions: General physical health deterioration, Non-cardiac chest pain, Multi-organ failure

Hepatobiliary Disorders: Hyperbilirubinemia

Infections and Infestations: Pneumocystis jiroveci pneumonia, Respiratory syncytial virus infection, Neutropenic sepsis, Bacteremia, Pneumonia respiratory syncytial viral, Cellulitis, Urosepsis, Septic shock, Clostridium difficile colitis, Pneumonia streptococcal, Lobar pneumonia, Viral infection, Lung infection

Investigations: Alanine aminotransferase increased, Hemoglobin decreased

Injury, poisoning and procedural complications: Fall, Compression fracture, Spinal compression fracture

Metabolism and nutritional disorders: Hyperkalemia, Failure to thrive

Nervous system disorders: Depressed level of consciousness, Syncope

Psychiatric disorders: Mental status change

Renal and urinary disorders: Urinary retention, Hyponatremia

Reproductive system and breast disorders: Pelvic pain

Respiratory, thoracic, and mediastinal disorders: Interstitial lung disease, Pulmonary embolism, Respiratory failure, Bronchospasm

Vascular disorders: Hypotension

Kaposi Sarcoma (KS)

The safety of POMALYST in patients with KS was evaluated in Trial 12-C-0047 [see Clinical Studies (14.2)]. Twenty-eight patients received POMALYST 5 mg taken orally once daily on Days 1 through 21 of repeated 28-day cycles. The study excluded patients with procoagulant disorders or a history of venous or arterial thromboembolism. Patients received DVT prophylaxis with daily low dose aspirin. Across all patients treated on Trial 12-C-0047, 75% were exposed to pomalidomide for 6 months or longer and 25% were exposed for greater than one year.

Serious adverse reactions occurred in 18% (5/28) of patients who received POMALYST. The following serious adverse reactions each occurred in 1 patient: anemia, decreased neutrophil count, and hematuria.

Permanent discontinuation due to an adverse reaction occurred in 11% (3/28) of patients who received POMALYST.

Dosage interruptions due to an adverse reaction occurred in 14% (4/28) of patients who received POMALYST. The most frequent adverse reaction requiring dosage interruption was decreased neutrophil count, which occurred in 3 patients.

The POMALYST dose was reduced due to an adverse reaction in 1 patient due to gout.

Tables 5 and 6 summarize the adverse reactions and select laboratory abnormalities reported in Trial 12-C-0047.

Table 5: Adverse Reactions (≥ 20%) in Patients Who Received POMALYST in Trial 12-C-0047
Adverse Reaction | Grades 1-4 N=28 % | Grade 3 or 4 N=28 %
Rash, maculo-papular | 71 | 3.6
Constipation | 71 | 0
Fatigue | 68 | 0
Nausea | 36 | 0
Diarrhea | 32 | 3.6
Cough | 29 | 0
Dyspnea | 29 | 0
Peripheral Edema | 29 | 3.6
Upper respiratory tract infection | 29 | 0
Muscle spasms | 25 | 0
Hypothyroidism | 21 | 0
Dry skin | 21 | 0
Chills | 21 | 0

Table 6: Frequency of Select Laboratory Abnormalities (≥ 10%) Worsening from Baseline in Patients Who Received POMALYST in Trial 12-C-0047
Laboratory Abnormality | Grades 1-4* % | Grades 3-4* %
Hematology
Decreased Absolute Neutrophil Count | 96 | 50
Decreased White Blood Cells | 79 | 3.6
Decreased Hemoglobin | 54 | 0
Decreased Platelets | 54 | 0
Chemistry
Elevated Creatinine | 86 | 3.6
Elevated Glucose | 57 | 7
Decreased Albumin | 54 | 0
Decreased Phosphate | 54 | 25
Decreased Calcium | 50 | 0
Increased Alanine Aminotransferase (ALT) | 32 | 0
Increased Aspartate Aminotransferase (AST) | 25 | 0
Elevated Creatine Kinase | 25 | 7
Decreased Magnesium | 14 | 0
Elevated Alkaline Phosphate | 14 | 3.6
* Denominator is the number of patients for whom there is a baseline and at least one post baseline assessment for the laboratory parameter.

6.2 Postmarketing Experience

The following adverse reactions have been identified during postapproval use of POMALYST. Because these reactions are reported voluntarily from a population of uncertain size, it is not always possible to reliably estimate their frequency or establish a causal relationship to drug exposure.

Blood and Lymphatic System Disorders: Pancytopenia

Endocrine Disorders: Hypothyroidism, hyperthyroidism

Gastrointestinal Disorders: Gastrointestinal hemorrhage

Hepatobiliary Disorders: Hepatic failure (including fatal cases), elevated liver enzymes

Immune system Disorders: Allergic reactions (e.g., angioedema, anaphylaxis, urticaria), solid organ transplant rejection

Infections and Infestations: Hepatitis B virus reactivation, Herpes zoster, progressive multifocal leukoencephalopathy (PML)

Neoplasms benign, malignant and unspecified (incl cysts and polyps): Tumor lysis syndrome, basal cell carcinoma, and squamous cell carcinoma of the skin

Skin and Subcutaneous Tissue Disorders: Stevens-Johnson Syndrome, toxic epidermal necrolysis, drug reaction with eosinophilia and systemic symptoms (DRESS)

7 DRUG INTERACTIONS

7.1 Drugs That Affect Pomalidomide Plasma Concentrations

CYP1A2 inhibitors:

In healthy subjects, co-administration of fluvoxamine, a strong CYP1A2 inhibitor, increased Cmax and AUC of pomalidomide by 24% and 125% respectively [see Clinical Pharmacology (12.3)]. Increased pomalidomide exposure may increase the risk of exposure related toxicities. Avoid co-administration of strong CYP1A2 inhibitors (e.g. ciprofloxacin and fluvoxamine). If co-administration is unavoidable, reduce the POMALYST dose [see Dosage and Administration (2.6)].

8 USE IN SPECIFIC POPULATIONS

8.1 Pregnancy

Pregnancy Exposure Registry

There is a pregnancy exposure registry that monitors pregnancy outcomes in females exposed to POMALYST during pregnancy as well as female partners of male patients who are exposed to POMALYST. This registry is also used to understand the root cause for the pregnancy. Report any suspected fetal exposure to POMALYST to the FDA via the MedWatch program at 1-800-FDA-1088 and also to the REMS Call Center at 1-888-423-5436.

Risk Summary

Based on the mechanism of action [see Clinical Pharmacology (12.1)] and findings from animal studies, POMALYST can cause embryo-fetal harm when administered to a pregnant female and is contraindicated during pregnancy [see Contraindications (4), and Warnings and Precautions (5.1)].

POMALYST is a thalidomide analogue. Thalidomide is a human teratogen, inducing a high frequency of severe and life-threatening birth defects such as amelia (absence of limbs), phocomelia (short limbs), hypoplasticity of the bones, absence of bones, external ear abnormalities (including anotia, micropinna, small or absent external auditory canals), facial palsy, eye abnormalities (anophthalmos, microphthalmos), and congenital heart defects. Alimentary tract, urinary tract, and genital malformations have also been documented, and mortality at or shortly after birth has been reported in about 40% of infants.

Pomalidomide was teratogenic in both rats and rabbits when administered during the period of organogenesis. Pomalidomide crossed the placenta after administration to pregnant rabbits (see Data). If this drug is used during pregnancy or if the patient becomes pregnant while taking this drug, the patient should be apprised of the potential risk to a fetus.

If pregnancy does occur during treatment, immediately discontinue the drug. Under these conditions, refer patient to an obstetrician/gynecologist experienced in reproductive toxicity for further evaluation and counseling. Report any suspected fetal exposure to POMALYST to the FDA via the MedWatch program at 1-800-FDA-1088 and also to the REMS Call Center at 1-888-423-5436.

The estimated background risk of major birth defects and miscarriage for the indicated population is unknown. The estimated background risk in the U.S. general population of major birth defects is 2%-4% and of miscarriage is 15%-20% of clinically recognized pregnancies.

Data

Animal Data

Pomalidomide was teratogenic in both rats and rabbits in the embryo-fetal developmental studies when administered during the period of organogenesis.

In rats, pomalidomide was administered orally to pregnant animals at doses of 25 to 1000 mg/kg/day. Malformations or absence of urinary bladder, absence of thyroid gland, and fusion and misalignment of lumbar and thoracic vertebral elements (vertebral, central, and/or neural arches) were observed at all dose levels. There was no maternal toxicity observed in this study. The lowest dose in rats resulted in an exposure (AUC) approximately 85-fold of the human exposure at the recommended dose of 4 mg/day. Other embryo-fetal toxicities included increased resorptions leading to decreased number of viable fetuses.

In rabbits, pomalidomide was administered orally to pregnant animals at doses of 10 to 250 mg/kg/day. Increased cardiac malformations such as interventricular septal defect were seen at all doses with significant increases at 250 mg/kg/day. Additional malformations observed at 250 mg/kg/day included anomalies in limbs (flexed and/or rotated fore- and/or hindlimbs, unattached or absent digit) and associated skeletal malformations (not ossified metacarpal, misaligned phalanx and metacarpal, absent digit, not ossified phalanx, and short not ossified or bent tibia), moderate dilation of the lateral ventricle in the brain, abnormal placement of the right subclavian artery, absent intermediate lobe in the lungs, low-set kidney, altered liver morphology, incompletely or not ossified pelvis, an increased average for supernumerary thoracic ribs, and a reduced average for ossified tarsals. No maternal toxicity was observed at the low dose (10 mg/kg/day) that resulted in cardiac anomalies in fetuses; this dose resulted in an exposure (AUC) approximately equal to that reported in humans at the recommended dose of 4 mg/day. Additional embryo-fetal toxicity included increased resorption.

Following daily oral administration of pomalidomide from Gestation Day 7 through Gestation Day 20 in pregnant rabbits, fetal plasma pomalidomide concentrations were approximately 50% of the maternal Cmax at all dosages (5 to 250 mg/kg/day), indicating that pomalidomide crossed the placenta.

8.2 Lactation

Risk Summary

There is no information regarding the presence of pomalidomide in human milk, the effects of POMALYST on the breastfed child, or the effects of POMALYST on milk production. Pomalidomide was excreted in the milk of lactating rats (see Data). Because many drugs are excreted in human milk and because of the potential for adverse reactions in a breastfed child from POMALYST, advise women not to breastfeed during treatment with POMALYST.

Data

Animal Data

Following a single oral administration of pomalidomide to lactating rats approximately 14 days postpartum, pomalidomide was transferred into milk, with milk to plasma ratios of 0.63 to 1.46.

8.3 Females and Males of Reproductive Potential

Pregnancy Testing

POMALYST can cause fetal harm when administered during pregnancy [see Use in Specific Populations (8.1)]. Verify the pregnancy status of females of reproductive potential prior to initiating POMALYST therapy and during therapy. Advise females of reproductive potential that they must avoid pregnancy 4 weeks before therapy, while taking POMALYST, during dose interruptions and for at least 4 weeks after completing therapy.

Females of reproductive potential must have 2 negative pregnancy tests before initiating POMALYST. The first test should be performed within 10-14 days, and the second test within 24 hours prior to prescribing POMALYST. Once treatment has started and during dose interruptions, pregnancy testing for females of reproductive potential should occur weekly during the first 4 weeks of use, then pregnancy testing should be repeated every 4 weeks in females with regular menstrual cycles. If menstrual cycles are irregular, the pregnancy testing should occur every 2 weeks. Pregnancy testing and counseling should be performed if a patient misses her period or if there is any abnormality in her menstrual bleeding. POMALYST treatment must be discontinued during this evaluation.

Contraception

Females

Females of reproductive potential must commit either to abstain continuously from heterosexual sexual intercourse or to use 2 methods of reliable birth control simultaneously: one highly effective form of contraception – tubal ligation, IUD, hormonal (birth control pills, injections, hormonal patches, vaginal rings, or implants), or partner's vasectomy, and 1 additional effective contraceptive method – male latex or synthetic condom, diaphragm, or cervical cap. Contraception must begin 4 weeks prior to initiating treatment with POMALYST, during therapy, during dose interruptions, and continuing for 4 weeks following discontinuation of POMALYST therapy. Reliable contraception is indicated even where there has been a history of infertility, unless due to hysterectomy. Females of reproductive potential should be referred to a qualified provider of contraceptive methods, if needed.

Males

Pomalidomide is present in the semen of males who take POMALYST. Therefore, males must always use a latex or synthetic condom during any sexual contact with females of reproductive potential while taking POMALYST and for up to 4 weeks after discontinuing POMALYST, even if they have undergone a successful vasectomy. Male patients taking POMALYST must not donate sperm.

Infertility

Based on findings in animals, female fertility may be compromised by treatment with POMALYST [see Nonclinical Toxicology (13.1)].

8.4 Pediatric Use

The safety and effectiveness of POMALYST have not been established in pediatric patients. The safety and effectiveness were assessed but not established in two open-label studies: a dose escalation study in 25 pediatric patients aged 5 to <17 with recurrent, progressive or refractory CNS tumors [NCT02415153] and a parallel-group study conducted in 47 pediatric patients aged 4 to <17 years with recurrent or progressive high-grade glioma, medulloblastoma, ependymoma, or diffuse intrinsic pontine glioma (DIPG) [NCT03257631]. No new safety signals were observed in pediatric patients across these studies.

At the same dose by body surface area, pomalidomide exposure in 55 pediatric patients aged 4 to < 17 years old was within the range observed in adult patients with MM but higher than the exposure observed in adult patients with KS [see Clinical Pharmacology (12.3)].

8.5 Geriatric Use

Multiple Myeloma

Of the total number of patients in clinical studies of POMALYST, 44% were aged older than 65 years, while 10% were aged older than 75 years. No overall differences in effectiveness were observed between these patients and younger patients. In these studies, patients older than 65 years were more likely than patients less than or equal to 65 years of age to experience pneumonia.

Kaposi Sarcoma

Of the 28 patients who received POMALYST, 11% were 65 years or older, and 3.6% were 75 years of age or older. The clinical study did not include sufficient numbers of patients aged 65 and over to determine whether they respond differently from younger patients.

8.6 Renal Impairment

In patients with severe renal impairment requiring dialysis, the AUC of pomalidomide increased by 38% and the rate of SAE increased by 64% relative to patients with normal renal function; therefore, starting dose adjustment is recommended. For patients with severe renal impairment requiring dialysis, administer POMALYST after the completion of hemodialysis on dialysis days because exposure of pomalidomide could be significantly decreased during dialysis [see Dosage and Administration (2.7) and Clinical Pharmacology (12.3)].

8.7 Hepatic Impairment

Pomalidomide is metabolized primarily by the liver. Following single dose administration, the AUC of pomalidomide increased 51%, 58%, and 72% in subjects with mild (Child-Pugh class A), moderate (Child-Pugh class B), and severe (Child-Pugh class C) hepatic impairment, respectively compared to subjects with normal liver function. Dose adjustment is recommended in patients with hepatic impairment [see Dosage and Administration (2.8) and Clinical Pharmacology (12.3)].

8.8 Smoking Tobacco

Cigarette smoking reduces pomalidomide AUC due to CYP1A2 induction. Advise patients that smoking may reduce the efficacy of pomalidomide [see Clinical Pharmacology (12.3)].

10 OVERDOSAGE

Hemodialysis can remove pomalidomide from circulation.

11 DESCRIPTION

Pomalidomide is a thalidomide analog. The chemical name is (RS)-4-Amino-2-(2,6-dioxo-piperidin-3-yl)-isoindoline-1,3-dione and it has the following chemical structure:

The empirical formula for pomalidomide is C13H11N3O4 and the gram molecular weight is 273.24.

Pomalidomide is a yellow solid powder. It has limited to low solubility into organic solvents and it has low solubility in all pH solutions (about 0.01 mg/mL). Pomalidomide has a chiral carbon atom which exists as a racemic mixture of the R(+) and S(-) enantiomers.

POMALYST is available in 1-mg, 2-mg, 3-mg, and 4-mg capsules for oral administration. Each capsule contains pomalidomide as the active ingredient and the following inactive ingredients: mannitol, pregelatinized starch, and sodium stearyl fumarate. The 1-mg capsule shell contains gelatin, titanium dioxide, FD&C blue 2, yellow iron oxide, white ink, and black ink. The 2-mg capsule shell contains gelatin, titanium dioxide, FD&C blue 2, yellow iron oxide, FD&C red 3, and white ink. The 3-mg capsule shell contains gelatin, titanium dioxide, FD&C blue 2, yellow iron oxide, and white ink. The 4-mg capsule shell contains gelatin, titanium dioxide, FD&C blue 1, FD&C blue 2, and white ink.

12 CLINICAL PHARMACOLOGY

12.1 Mechanism of Action

Pomalidomide is an analogue of thalidomide with immunomodulatory, antiangiogenic, and antineoplastic properties. Cellular activities of pomalidomide are mediated through its target cereblon, a component of a cullin ring E3 ubiquitin ligase enzyme complex. In vitro, in the presence of drug, substrate proteins (including Aiolos and Ikaros) are targeted for ubiquitination and subsequent degradation leading to direct cytotoxic and immunomodulatory effects. In in vitro cellular assays, pomalidomide inhibited proliferation and induced apoptosis of hematopoietic tumor cells. Additionally, pomalidomide inhibited the proliferation of lenalidomide-resistant multiple myeloma (MM) cell lines and synergized with dexamethasone in both lenalidomide-sensitive and lenalidomide-resistant cell lines to induce tumor cell apoptosis. Pomalidomide enhanced T cell- and natural killer (NK) cell-mediated immunity and inhibited production of pro-inflammatory cytokines (e.g., TNF-α and IL-6) by monocytes. Pomalidomide demonstrated anti-angiogenic activity in a mouse tumor model and in the in vitro umbilical cord model.

12.2 Pharmacodynamics

Pomalidomide exposure-response analyses showed that there was no relationship between systemic pomalidomide exposure level and efficacy or safety following pomalidomide dose of 4 mg.

Cardiac Electrophysiology

The QTc prolongation potential of pomalidomide was evaluated in a single center, randomized, double-blind crossover study (N=72) using 4 mg pomalidomide, 20 mg pomalidomide, placebo, and 400 mg moxifloxacin (positive control). No significant QTc prolongation effect of pomalidomide was observed following pomalidomide doses of 4 and 20 mg.

12.3 Pharmacokinetics

In patients with MM who received POMALYST 4 mg daily alone or in combination with dexamethasone, pomalidomide steady-state drug exposure was characterized by AUC (CV%) of 860 (37%) ng∙h/mL and Cmax (CV%) of 75 (32%) ng/mL. In patients with Kaposi sarcoma (KS) who received POMALYST 5 mg daily, pomalidomide steady-state drug exposure was characterized by AUC of 462.3 ng∙h/mL (82%) and Cmax of 53.1 ng/mL (50%).

Absorption

Following administration of single oral doses of POMALYST, the maximum plasma concentration (Cmax) for pomalidomide occurs at 2 to 3 hours postdose in patients with MM or KS.

Effect of Food

Co-administration of POMALYST with a high-fat meal (approximately 50% of the total caloric content) and high-calorie meal (approximately 800 to 1000 calories) (the meal contained approximately 150, 250, and 500 to 600 calories from protein, carbohydrates, and fat, respectively) delays the Tmax by 2.5 hours, decreased mean plasma Cmax and AUC in healthy subjects by about 27% and 8%, respectively.

Distribution

Pomalidomide has a mean apparent volume of distribution (Vd/F) between 62 and 138 L at steady state in patients with MM or KS.

Pomalidomide is distributed in semen of healthy subjects at a concentration of approximately 67% of plasma level at 4 hours postdose (~Tmax) after 4 days of 2 mg once-daily dosing.

Human plasma protein binding of pomalidomide ranges from 12% to 44% and is not concentration dependent. Pomalidomide is a substrate for P-gp.

Elimination

Pomalidomide has a mean total body clearance (CL/F) of 7-10 L/h in patients with MM or KS. Pomalidomide is eliminated with a median plasma half-life of 9.5 hours in healthy subjects and 7.5 hours in patients with MM or KS.

Metabolism

Pomalidomide is primarily metabolized in the liver by CYP1A2 and CYP3A4. Minor contributions from CYP2C19 and CYP2D6 were also observed in vitro.

Excretion

Following a single oral administration of [^14C]-pomalidomide to healthy subjects, approximately 73% and 15% of the radioactive dose was eliminated in urine and feces, respectively, with approximately 2% and 8% of the radiolabeled dose eliminated unchanged as pomalidomide in urine and feces.

Specific Populations

Age (61 to 85 years old), sex and race have no clinically significant effect on the systemic exposure of pomalidomide.

Patients with Renal Impairment

Pomalidomide pharmacokinetic parameters were not significantly affected in patients with moderate (30 mL/min ≤ CLcr< 60 mL/min) or severe (15 mL/min ≤ CLcr< 30 mL/min) renal impairment relative to patients with normal renal function (CLcr ≥ 60 mL/min). Mean exposure (AUC) to pomalidomide increased by 38% in patients with severe renal impairment requiring dialysis (CLcr< 30 mL/min requiring dialysis) and 40% in patients with end stage renal disease (CLcr< 15 mL/min) on non-dialysis days. In patients with severe renal impairment requiring dialysis, the estimated dialysis clearance is approximately 12 L/h which is higher than pomalidomide total body clearance, indicating hemodialysis will remove pomalidomide from the blood circulation.

Patients with Hepatic Impairment

Mean exposure (AUC) of pomalidomide increased by 51%, 58% and 72% in subjects with mild, moderate or severe hepatic impairment as defined by Child-Pugh criteria, respectively.

Drug Interaction Studies

Clinical Studies

Co-administration of POMALYST with the following drugs did not increase pomalidomide exposure to a clinically significant extent: ketoconazole (a strong CYP3A4 and P-gp inhibitor), carbamazepine (a strong CYP3A4 inducer) and dexamethasone (a weak to moderate CYP3A4 inducer). Co-administration of POMALYST with drugs that are CYP1A2 inducers has not been studied.

CYP1A2 Inhibitors: Co-administration of fluvoxamine (a strong CYP1A2 inhibitor) with POMALYST increased mean [90% confidence interval] pomalidomide exposure by 125% [98% to 157%] compared to POMALYST alone in healthy subjects. Co-administration of fluvoxamine in the presence of ketoconazole (a strong CYP3A4 and P-gp inhibitor) with POMALYST increased mean pomalidomide exposure by 146% [126% to 167%] compared to POMALYST administered alone in healthy subjects, indicating the predominant effect of CYP1A2 inhibition in the increase of pomalidomide exposure [see Dosage and Administration (2.6) and Drug Interactions (7.1)].

Strong CYP3A4 and P-gp Inhibitors: Co-administration of ketoconazole (a strong CYP3A4 and P-gp inhibitor) in 16 healthy male subjects increased AUC of pomalidomide by 19% compared to POMALYST administered alone.

Strong CYP1A2 Inducers: Co-administration of POMALYST with drugs that are CYP1A2 inducers has not been studied and may reduce pomalidomide exposure.

Strong CYP3A4 Inducers: Co-administration of carbamazepine to 16 healthy male subjects decreased AUC of pomalidomide by 20% with a 90% confidence interval [13% to 27%] compared to when pomalidomide was administered alone.

Dexamethasone: Co-administration of multiple doses of 4 mg POMALYST with 20 mg to 40 mg dexamethasone (a weak to moderate inducer of CYP3A4) to patients with MM had no effect on the pharmacokinetics of pomalidomide compared to when pomalidomide was administered alone.

Smoking: In 14 healthy male subjects who smoked 25 cigarettes per day for a total of 10 days, after single oral dose of 4 mg POMALYST, Cmax of pomalidomide increased 14% while AUC of pomalidomide decreased 32%, compared to that in 13 healthy male subjects who were non-smokers.

In Vitro Studies

Pomalidomide does not inhibit or induce cytochrome p450 enzymes or transporters in vitro.

13 NONCLINICAL TOXICOLOGY

13.1 Carcinogenesis, Mutagenesis, Impairment of Fertility

Studies examining the carcinogenic potential of pomalidomide have not been conducted. One of 12 monkeys dosed with 1 mg/kg of pomalidomide (an exposure approximately 15-fold of the exposure in patients at the recommended dose of 4 mg/day) developed acute myeloid leukemia in a 9-month repeat-dose toxicology study.

Pomalidomide was not mutagenic or clastogenic in a battery of tests, including the bacteria reverse mutation assay (Ames test), the in vitro assay using human peripheral blood lymphocytes, and the micronucleus test in orally treated rats administered doses up to 2000 mg/kg/day.

In a fertility and early embryonic development study in rats, drug-treated males were mated with untreated or treated females. Pomalidomide was administered to males and females at doses of 25 to 1000 mg/kg/day. When treated males were mated with treated females, there was an increase in post-implantation loss and a decrease in mean number of viable embryos at all dose levels. There were no other effects on reproductive functions or the number of pregnancies. The lowest dose tested in animals resulted in an exposure (AUC) approximately 100-fold of the exposure in patients at the recommended dose of 4 mg/day. When treated males in this study were mated with untreated females, all uterine parameters were comparable to the controls. Based on these results, the observed effects were attributed to the treatment of females.

14 CLINICAL STUDIES

14.1 Multiple Myeloma

Trial 1

Trial 1 was a phase 2, multicenter, randomized open-label study in patients with relapsed multiple myeloma (MM) who were refractory to their last myeloma therapy and had received lenalidomide and bortezomib. Patients were considered relapsed if they had achieved at least stable disease for at least 1 cycle of treatment to at least 1 prior regimen and then developed progressive disease. Patients were considered refractory if they experienced disease progression on or within 60 days of their last therapy. A total of 221 patients were randomized to receive POMALYST alone or POMALYST with Low-dose Dex. In Trial 1, the safety and efficacy of POMALYST 4 mg, once daily for 21 of 28 days, until disease progression, were evaluated alone and in combination with Low-dose Dex (40 mg/day given only on Days 1, 8, 15, and 22 of each 28-day cycle for patients aged 75 years or younger, or 20 mg/day given only on Days 1, 8, 15, and 22 of each 28-day cycle for patients aged greater than 75 years). Patients in the POMALYST alone arm were allowed to add Low-dose Dex upon disease progression.

Table 7 summarizes the baseline patient and disease characteristics in Trial 1. The baseline demographics and disease characteristics were balanced and comparable between the study arms.

Table 7: Baseline Demographic and Disease-Related Characteristics – Trial 1
 | POMALYST (n=108) | POMALYST + Low-dose Dex (n=113)
Patient Characteristics
Median age, years (range) | 61 (37-88) | 64 (34-88)
Age distribution, n (%)
<65 years | 65 (60.2) | 60 (53.1)
≥65 years | 43 (39.8) | 53 (46.9)
Sex, n (%)
Male | 57 (52.8) | 62 (54.9)
Female | 51 (47.2) | 51 (45.1)
Race/ethnicity, n (%)
White | 86 (79.6) | 92 (81.4)
Black or African American | 16 (14.8) | 17 (15)
All other race | 6 (5.6) | 4 (3.6)
ECOG Performance, n (%)
Status 0-1 | 95 (87.9) | 100 (88.5)
Disease Characteristics
Number of prior therapies
Median (min, max) | 5 (2, 12) | 5 (2, 13)
Prior transplant, n (%) | 82 (75.9) | 84 (74.3)
Refractory to bortezomib and lenalidomide, n (%) | 64 (59.3) | 69 (61.1)
Data cutoff: 01 April 2011

Table 8 summarizes the analysis results of overall response rate (ORR) and duration of response (DOR), based on assessments by the Independent Review Adjudication Committee for the treatment arms in Trial 1. ORR did not differ based on type of prior antimyeloma therapy.

Table 8: Trial 1 Results
 | POMALYSTa (n=108) | POMALYST + Low-dose Dex (n=113)
Response
Overall Response Rate (ORR),b n (%) | 8 (7.4) | 33 (29.2)
95% CI for ORR (%) | (3.3, 14.1) | (21.0, 38.5)
Complete Response (CR), n (%) | 0 (0.0) | 1 (0.9)
Partial Response (PR), n (%) | 8 (7.4) | 32 (28.3)
Duration of Response (DOR)
Median, months | NE | 7.4
95% CI for DOR (months) | NE | (5.1, 9.2)
a Results are prior to the addition of dexamethasone.
b ORR = PR + CR per EBMT criteria.
CI, confidence interval; NE, not established (the median has not yet been reached).
Data cutoff: 01 April 2011

Trial 2

Trial 2 was a Phase 3 multi-center, randomized, open-label study, where POMALYST + Low-dose Dex therapy was compared to High-dose Dex in adult patients with relapsed and refractory MM, who had received at least two prior treatment regimens, including lenalidomide and bortezomib, and demonstrated disease progression on or within 60 days of the last therapy. Patients with creatinine clearance ≥ 45mL/min qualified for the trial. A total of 455 patients were enrolled in the trial: 302 in the POMALYST + Low-dose Dex arm and 153 in the High-dose Dex arm. Patients in the POMALYST + Low-dose Dex arm were administered 4 mg POMALYST orally on Days 1 to 21 of each 28-day cycle. Dexamethasone (40 mg) was administered once per day on Days 1, 8, 15 and 22 of a 28-day cycle. Patients > 75 years of age started treatment with 20 mg dexamethasone using the same schedule. For the High-dose Dex arm, dexamethasone (40 mg) was administered once per day on Days 1 through 4, 9 through 12, and 17 through 20 of a 28-day cycle. Patients > 75 years of age started treatment with 20 mg dexamethasone using the same schedule. Treatment continued until patients had disease progression.

Baseline patient and disease characteristics were balanced and comparable between the study arms, as summarized in Table 9. Overall, 94% of patients had disease refractory to lenalidomide, 79% had disease refractory to bortezomib and 74% had disease refractory to both lenalidomide and bortezomib.

Table 9: Baseline Demographic and Disease-Related Characteristics – Trial 2
 | POMALYST + Low-dose Dex | High-dose Dex
 | (N=302) | (N=153)
Patient Characteristics
Median Age, years (range) | 64 (35, 84) | 65 (35, 87)
Age Distribution n (%)
< 65 years | 158 (52) | 74 (48)
≥ 65 years | 144 (48) | 79 (52)
Sex n (%)
Male | 181 (60) | 87 (57)
Female | 121 (40) | 66 (43)
Race/Ethnicity n (%)
White | 244 (81) | 113 (74)
Black or African American | 4 (1) | 3 (2)
Asian | 4 (1) | 0 (0)
Other Race | 2 (1) | 2 (1)
Not Collected | 48 (16) | 35 (23)
ECOG Performance n (%)
Status 0 | 110 (36) | 36 (24)
Status 1 | 138 (46) | 86 (56)
Status 2 | 52 (17) | 25 (16)
Status 3 | 0 (0) | 3 (2)
Missing | 2 (1) | 3 (2)
Disease Characteristics
Number of Prior Therapies
Median, (Min, Max) | 5 (2, 14) | 5 (2, 17)
Prior stem cell transplant n (%) | 214 (71) | 105 (69)
Refractory to bortezomib and lenalidomide n (%) | 225 (75) | 113 (74)
Data cutoff: 01March 2013

Table 10 summarizes the progression free survival (PFS) and overall response rate (ORR) based on the assessment by the Independent Review Adjudication Committee (IRAC) review at the final PFS analysis and overall survival (OS) at the OS analysis. PFS was significantly longer with POMALYST + Low-dose Dex than High-dose Dex: HR 0.45 (95% CI: 0.35-0.59 p < 0.001). OS was also significantly longer with POMALYST + Low-dose Dex than High-dose Dex: HR 0.70 (95% CI: 0.54-0.92 p = 0.009). The Kaplan-Meier curves for PFS and OS for the ITT population are provided in Figures 1 and 2, respectively.

Table 10: Trial 2 Results
 | POMALYST + Low-dose Dex | High-dose Dex
 | (N=302) | (N=153)
Progression Free Survival Time
Number (%) of events | 164 (54.3) | 103 (67.3)
Mediana (2-sided 95% CI) (months) | 3.6 [3.0, 4.6] | 1.8 [1.6, 2.1]
Hazard Ratio (Pom+LD-Dex:HD-Dex) 2-Sided 95% CIb | 0.45 [0.35, 0.59]
Log-Rank Test 2-sided P-Valuec | <0.001
Overall Survival Timed
Number (%) of deaths | 147 (48.7) | 86 (56.2)
Mediana (2-sided 95% CI) (months) | 12.4 [10.4, 15.3] | 8.0 [6.9, 9.0]
Hazard Ratio (Pom+LD-Dex:HD-Dex) 2-Sided 95% CIe | 0.70 [0.54, 0.92]
Log-Rank Test 2-sided P-Value f, g | 0.009
Overall Response Rate, n (%) | 71 (23.5) | 6 (3.9)
Complete Response | 1 (0.3) | 0
Very Good Partial Response | 8 (2.6) | 1 (0.7)
Partial Response | 62 (20.5) | 5 (3.3)
Note: CI=Confidence interval; HD-Dex=High dose dexamethasone; IRAC=Independent Review Adjudication Committee; LD-Dex=Low dose dexamethasone.
a The median is based on Kaplan-Meier estimate.
b Based on Cox proportional hazards model comparing the hazard functions associated with treatment groups, stratified by age (≤75 vs >75), diseases population (refractory to both Lenalidomide and Bortezomib vs not refractory to both drugs), and prior number of antimyeloma therapy (=2 vs >2), stratification factors for the trial.
c The p-value is based on a stratified log-rank test with the same stratification factors as the above Cox model.
d 53% of patients in the High-dose Dex arm subsequently received POMALYST.
e Based on Cox proportional hazards model (unstratified) comparing the hazard functions associated with treatment groups.
f The p-value is based on an unstratified log-rank test.
g Alpha control for PFS and OS.
Data cutoff: 07 Sep 2012 for PFS
Data cutoff: 01 Mar 2013 for OS and ORR

Figure 1: Progression Free Survival Based on IRAC Review of Response by IMWG Criteria (Stratified Log Rank Test) (ITT Population)

Data cut-off: 07 Sep 2012

Figure 2: Kaplan-Meier Curve of Overall Survival (ITT Population)

Data cutoff: 01 Mar 2013

14.2 Kaposi Sarcoma

The clinical trial 12-C-0047 (NCT01495598), was an open label, single center, single arm clinical study that evaluated the safety and efficacy of POMALYST in patients with Kaposi sarcoma (KS). A total of 28 patients (18 HIV-positive, 10 HIV-negative) received POMALYST 5 mg orally once daily on Days 1 through 21 of each 28-day cycle until disease progression or unacceptable toxicity. All HIV-positive patients continued highly active antiretroviral therapy (HAART). The trial excluded patients with symptomatic pulmonary or visceral KS, history of venous or arterial thromboembolism, or procoagulant disorders. Patients received thromboprophylaxis with aspirin 81 mg once daily throughout therapy.

The median age was 52.5 years, all were male, 75% were White, and 14% Black or African American. Seventy-five percent of patients had advanced disease (T1) at the time of enrollment, 11% had ≥ 50 lesions, and 75% had received prior chemotherapy.

The major efficacy outcome measure was overall response rate (ORR), which included complete response (CR), clinical complete response (cCR), and partial response (PR). Response was assessed by the investigator according to the AIDS Clinical Trial Group (ACTG) Oncology Committee response criteria for KS. The median time to first response was 1.8 months (0.9 to 7.6). Efficacy results are presented in Table 11.

Table 11: Trial 12-C-0047 Results
 | All Patients N=28 | HIV-Positive N=18 | HIV-Negative N=10
ORR ^1, n (%) | 20 (71) | 12 (67) | 8 (80)
[95% CI] | [51, 87] | (41, 87) | (44, 98)
CR ^1, n (%) | 4 (14) | 3 (17) | 1 (10)
PR, n (%) | 16 (57) | 9 (50) | 7 (70)
Duration of Response, KS ^2, | 12.1 | 12.5 | 10.5
Median in months [95% CI]^3 | [7.6, 16.8] | [6.5, 24.9] | [3.9, 24.2]
Duration of Response, KS (%)
Percent greater than 12 months | 50 | 58 | 38
Percent greater than 24 months | 20 | 17 | 25
CI: confidence interval, ORR: overall response rate, CR: complete response, PR: partial response
^1 CR includes one HIV-negative patient who achieved a cCR.
^2 Calculated as date of first documented response to date of first documented disease progression, receipt of new treatment or second course of treatment, or death due to any cause, whichever occurs first. Median estimate is from Kaplan-Meier analysis.
^3 From Kaplan-Meier analysis.

15 REFERENCES

1. OSHA Hazardous Drugs. OSHA. http://www.osha.gov/SLTC/hazardousdrugs/index.html

16 HOW SUPPLIED/STORAGE AND HANDLING

Dark blue opaque cap and yellow opaque body, imprinted "POML" on the cap in white ink and "1 mg" on the body in black ink

 | 1 mg bottles of 21 | (NDC 59572-501-21)
 | 1 mg bottles of 100 | (NDC 59572-501-00)

Dark blue opaque cap and orange opaque body, imprinted "POML" on the cap and "2 mg" on the body in white ink

 | 2 mg bottles of 21 | (NDC 59572-502-21)
 | 2 mg bottles of 100 | (NDC 59572-502-00)

Dark blue opaque cap and green opaque body, imprinted "POML" on the cap and "3 mg" on the body in white ink

 | 3 mg bottles of 21 | (NDC 59572-503-21)
 | 3 mg bottles of 100 | (NDC 59572-503-00)

Dark blue opaque cap and blue opaque body, imprinted "POML" on the cap and "4 mg" on the body in white ink

 | 4 mg bottles of 21 | (NDC 59572-504-21)
 | 4 mg bottles of 100 | (NDC 59572-504-00)

STORAGE AND HANDLING

Store at 20°C-25°C (68°F-77°F); excursions permitted to 15°C-30°C (59°F-86°F) [see USP Controlled Room Temperature].

Care should be exercised in handling of POMALYST. Do not open or crush POMALYST capsules. If powder from POMALYST contacts the skin, wash the skin immediately and thoroughly with soap and water. If POMALYST contacts the mucous membranes, flush thoroughly with water.

Follow procedures for proper handling and disposal of hazardous drugs. ^1

17 PATIENT COUNSELING INFORMATION

Advise the patient to read the FDA-approved patient labeling (Medication Guide).

Embryo-Fetal Toxicity

Advise patients that POMALYST is contraindicated in pregnancy [see Contraindications (4)]. POMALYST is a thalidomide analogue and may cause serious birth defects or death to a developing baby [see Warnings and Precautions (5.1) and Use in Specific Populations (8.1)].

- Advise females of reproductive potential that they must avoid pregnancy while taking POMALYST and for at least 4 weeks after completing therapy.
- Initiate POMALYST treatment in females of reproductive potential only following a negative pregnancy test.
- Advise females of reproductive potential of the importance of monthly pregnancy tests and the need to use 2 different forms of contraception, including at least 1 highly effective form, simultaneously during POMALYST therapy, during dose interruptions, and for 4 weeks after she has completely finished taking POMALYST. Highly effective forms of contraception other than tubal ligation include IUD and hormonal (birth control pills, injections, patch, or implants) and a partner's vasectomy. Additional effective contraceptive methods include latex or synthetic condom, diaphragm, and cervical cap.
- Instruct patient to immediately stop taking POMALYST and contact her healthcare provider if she becomes pregnant while taking this drug, if she misses her menstrual period or experiences unusual menstrual bleeding, if she stops taking birth control, or if she thinks FOR ANY REASON that she may be pregnant.
- Advise patient that if her healthcare provider is not available, she should call the REMS Call Center at 1-888-423-5436 [see Warnings and Precautions (5.1) and Use in Specific Populations (8.3)].
- Advise males to always use a latex or synthetic condom during any sexual contact with females of reproductive potential while taking POMALYST and for up to 4 weeks after discontinuing POMALYST, even if they have undergone a successful vasectomy.
- Advise male patients taking POMALYST that they must not donate sperm [see Warnings and Precautions (5.1) and Use in Specific Populations (8.3)].
- All patients must be instructed to not donate blood while taking POMALYST and for 4 weeks following discontinuation of POMALYST [see Warnings and Precautions (5.1)].

PS-Pomalidomide REMS

Because of the risk of embryo-fetal toxicity, POMALYST is only available through a restricted program called PS-Pomalidomide REMS [see Warnings and Precautions (5.2)].

- Patients must sign a Patient-Physician Agreement Form and comply with the requirements to receive POMALYST. In particular, females of reproductive potential must comply with the pregnancy testing, contraception requirements, and participate in monthly telephone surveys. Males must comply with the contraception requirements [see Use in Specific Populations (8.3)].
- POMALYST is available only from pharmacies that are certified in PS-Pomalidomide REMS. Provide patients with the telephone number and website for information on how to obtain the product.

Pregnancy Exposure Registry

Inform females that there is a Pregnancy Exposure Registry that monitors pregnancy outcomes in females exposed to POMALYST during pregnancy and that they can contact the Pregnancy Exposure Registry by calling 1-888-423-5436 [see Use in Specific Populations (8.1)].

Venous and Arterial Thromboembolism

Inform patients of the risk of developing DVT, PE, MI, and stroke and to report immediately any signs and symptoms suggestive of these events for evaluation [see Warnings and Precautions (5.3)].

Hematologic Toxicities

Inform patients on the risks of developing neutropenia, thrombocytopenia, and anemia and the need to report signs and symptoms associated with these events to their healthcare provider for further evaluation [see Warnings and Precautions (5.5)].

Hepatotoxicity

Inform patients on the risks of developing hepatotoxicity, including hepatic failure and death, and to report signs and symptoms associated with these events to their healthcare provider for evaluation [see Warnings and Precautions (5.6)].

Severe Cutaneous Reactions

Inform patients of the potential risk for severe skin reactions such as SJS, TEN and DRESS and to report any signs and symptoms associated with these reactions to their healthcare provider for evaluation [see Warnings and Precautions (5.7)].

Dizziness and Confusional State

Inform patients of the potential risk of dizziness and confusional state with the drug, to avoid situations where dizziness or confusional state may be a problem, and not to take other medications that may cause dizziness or confusional state without adequate medical advice [see Warnings and Precautions (5.8)].

Neuropathy

Inform patients of the risk of neuropathy and to report the signs and symptoms associated with these events to their healthcare provider for further evaluation [see Warnings and Precautions (5.9)].

Second Primary Malignancies

Inform the patient that the potential risk of developing acute myelogenous leukemia during treatment with POMALYST is unknown [see Warnings and Precautions (5.10)].

Tumor Lysis Syndrome

Inform patients of the potential risk of tumor lysis syndrome and to report any signs and symptoms associated with this event to their healthcare provider for evaluation [see Warnings and Precautions (5.11)].

Hypersensitivity

Inform patients of the potential for severe hypersensitivity reactions such as angioedema and anaphylaxis to POMALYST. Instruct patients to contact their healthcare provider right away for any signs and symptoms of these reactions. Advise patients to seek emergency medical attention for signs or symptoms of severe hypersensitivity reactions [see Warnings and Precautions (5.12)].

Smoking Tobacco

Advise patients that smoking tobacco may reduce the efficacy of POMALYST [see Use in Specific Populations (8.8) and Clinical Pharmacology (12.3)].

Dosing Instructions

Inform patients on how to take POMALYST [see Dosage and Administration (2.2, 2.3, 2.9)]

- POMALYST should be taken once daily at about the same time each day.
- Patients on hemodialysis should take POMALYST following hemodialysis, on hemodialysis days.
- POMALYST may be taken with or without food.
- The capsules should not be opened, broken, or chewed. POMALYST should be swallowed whole with water.
- Instruct patients that if they miss a dose of POMALYST, they may still take it up to 12 hours after the time they would normally take it. If more than 12 hours have elapsed, they should be instructed to skip the dose for that day. The next day, they should take POMALYST at the usual time. Warn patients not to take 2 doses to make up for the one that they missed.

Marketed by: Bristol-Myers Squibb Company
Princeton, NJ 08543 USA

POMALYST® is a trademark of Celgene Corporation, a Bristol-Myers Squibb company.
POMPI.017/MG.015

MEDICATION GUIDE
POMALYST® (POM-uh-list)
(pomalidomide)
capsules

What is the most important information I should know about POMALYST?

Before you begin taking POMALYST, you must read and agree to all of the instructions in PS-Pomalidomide REMS. For more information, call 1-888-423-5436 or go to www.PS-PomalidomideREMS.com. Before prescribing POMALYST, your healthcare provider will explain PS-Pomalidomide REMS to you and have you sign the Patient-Physician Agreement Form.

POMALYST can cause serious side effects including:

- Possible birth defects (deformed babies) or death of an unborn baby. Females who are pregnant or who plan to become pregnant must not take POMALYST.
  POMALYST is similar to the medicine thalidomide (THALOMID). We know thalidomide can cause severe life-threatening birth defects. POMALYST has not been tested in pregnant females. POMALYST has harmed unborn animals in animal testing.

Females must not get pregnant:

  ∘ For at least 4 weeks before starting POMALYST
  ∘ While taking POMALYST
  ∘ During any breaks (interruptions) in your treatment with POMALYST
  ∘ For at least 4 weeks after stopping POMALYST

Females who can become pregnant:

  ∘ Will have pregnancy tests weekly for 4 weeks, then every 4 weeks if your menstrual cycle is regular, or every 2 weeks if your menstrual cycle is irregular.
    If you miss your period or have unusual bleeding, you will need to have a pregnancy test and receive counseling.
  ∘ Must agree to use two acceptable forms of birth control at the same time, for at least 4 weeks before, while taking, during any breaks (interruptions) in your treatment, and for at least 4 weeks after stopping POMALYST.
  ∘ Talk with your healthcare provider to find out about options for acceptable forms of birth control that you may use to prevent pregnancy before, during, and after treatment with POMALYST.

If you become pregnant while taking POMALYST, stop taking it right away and call your healthcare provider. If your healthcare provider is not available, you can call the REMS Call Center at 1-888-423-5436.
Healthcare providers and patients should report all cases of pregnancy to:

  ∘ FDA MedWatch at 1-800-FDA-1088, and
  ∘ REMS Call Center at 1-888-423-5436

There is a pregnancy exposure registry that monitors the outcomes of females who take POMALYST during pregnancy, or if their male partner takes POMALYST and they are exposed during pregnancy. You can enroll in this registry by calling the REMS Call Center at the phone number listed above.

POMALYST can pass into human semen:

  ∘ Males, including those who have had a vasectomy, must always use a latex or synthetic condom during any sexual contact with a pregnant female or a female that can become pregnant while taking POMALYST, during any breaks (interruptions) in your treatment with POMALYST, and for 4 weeks after stopping POMALYST.
  ∘ Do not have unprotected sexual contact with a female who is or could become pregnant. Tell your healthcare provider if you do have unprotected sexual contact with a female who is or could become pregnant.
  ∘ Do not donate sperm while taking POMALYST, during any breaks (interruptions) in your treatment, and for 4 weeks after stopping POMALYST. If a female becomes pregnant with your sperm, the baby may be exposed to POMALYST and may be born with birth defects.

Men, if your female partner becomes pregnant, you should call your healthcare provider right away.

- Blood clots in your arteries, veins, and lungs, heart attack, and stroke can happen if you take POMALYST. Most people who take POMALYST will also take a blood thinner medicine to help prevent blood clots.
  Before taking POMALYST, tell your healthcare provider:
  ∘ If you have had a blood clot in the past
  ∘ If you have high blood pressure, smoke, or if you have been told you have a high level of fat in your blood (hyperlipidemia)
  ∘ About all the medicines you take. Certain other medicines can also increase your risk for blood clots
    Call your healthcare provider or get medical help right away if you get any of the following during treatment with POMALYST:
    - Signs or symptoms of a blood clot in the lung, arm, or leg may include: shortness of breath, chest pain, or arm or leg swelling
    - Signs or symptoms of a heart attack may include: chest pain that may spread to the arms, neck, jaw, back, or stomach area (abdomen), feeling sweaty, shortness of breath, feeling sick or vomiting
    - Signs or symptoms of stroke may include: sudden numbness or weakness, especially on one side of the body, severe headache or confusion, or problems with vision, speech, or balance.

What is POMALYST?

POMALYST is a prescription medicine used to treat adults with:

- Multiple myeloma. POMALYST is taken along with the medicine dexamethasone, in people who:
  - have received at least 2 prior medicines to treat multiple myeloma, including a type of medicine known as a proteasome inhibitor and lenalidomide, and
  - their disease has become worse during treatment or within 60 days of finishing the last treatment.
- AIDS-related Kaposi sarcoma (KS). POMALYST is taken when highly active antiretroviral therapy (HAART) has not worked well enough or stopped working (failed).
- KS who do not have HIV infection (HIV negative).

It is not known if POMALYST is safe and effective in children.

Who should not take POMALYST?

Do not take POMALYST if you:

- are pregnant, plan to become pregnant, or become pregnant during treatment with POMALYST. See "What is the most important information I should know about POMALYST?"
- are allergic to pomalidomide or any of the ingredients in POMALYST. See the end of this Medication Guide for a complete list of ingredients in POMALYST.

What should I tell my healthcare provider before taking POMALYST?

Before you take POMALYST, tell your healthcare provider if you:

- smoke cigarettes. POMALYST may not work as well in people who smoke
- have liver problems
- have kidney problems and are receiving hemodialysis treatment
- have any other medical conditions
- are breastfeeding. You should not breastfeed during treatment with POMALYST. It is not known if POMALYST passes into your breast milk and can harm your baby.

Tell your healthcare provider about all the medicines you take, including prescription and over-the-counter medicines, vitamins, and herbal supplements. POMALYST and other medicines may affect each other, causing serious side effects. Talk with your healthcare provider before taking any new medicines.

Know the medicines you take. Keep a list of them to show your healthcare provider and pharmacist.

How should I take POMALYST?

- Take POMALYST exactly as prescribed and follow all the instructions of PS-Pomalidomide REMS.
- Swallow POMALYST capsules whole with water 1 time a day. Do not break, chew, or open your capsules.
- POMALYST may be taken with or without food.
- Take POMALYST at about the same time each day.
- If you are on hemodialysis, take POMALYST after hemodialysis, on hemodialysis days.
- Do not open the POMALYST capsules or handle them any more than needed. If you touch a broken POMALYST capsule or the medicine in the capsule, wash the area of your body right away with soap and water.
- If you miss a dose of POMALYST and it has been less than 12 hours since your regular time, take it as soon as you remember. If it has been more than 12 hours, just skip your missed dose. Do not take 2 doses at the same time.
- If you take too much POMALYST, call your healthcare provider right away.

What should I avoid while taking POMALYST?

- See "What is the most important information I should know about POMALYST?"
- Females: Do not get pregnant and do not breastfeed while taking POMALYST.
- Males: Do not donate sperm.
- Do not share POMALYST with other people. It may cause birth defects and other serious problems.
- Do not donate blood while you take POMALYST, during any breaks (interruptions) in your treatment, and for 4 weeks after stopping POMALYST. If someone who is pregnant gets your donated blood, her baby may be exposed to POMALYST and may be born with birth defects.
- POMALYST can cause dizziness and confusion. Avoid taking other medicines that may cause dizziness and confusion during treatment with POMALYST. Avoid situations that require you to be alert until you know how POMALYST affects you.

What are the possible side effects of POMALYST?

POMALYST can cause serious side effects, including:

- See "What is the most important information I should know about POMALYST?"
- Low white blood cells (neutropenia), low platelets (thrombocytopenia), and low red blood cells (anemia) are common with POMALYST, but can also be serious. You may need a blood transfusion or certain medicines if your blood counts drop too low. Your blood counts should be checked weekly for the first 8 weeks of treatment and monthly after that.
- Severe liver problems, including liver failure and death. Your healthcare provider should do blood tests to check your liver function during your treatment with POMALYST. Tell your healthcare provider right away if you develop any of the following symptoms of liver problems:

- Yellowing of your skin or the white part of your eyes (jaundice)
- Dark or brown (tea-colored) urine

- Pain on the upper right side of your stomach area (abdomen)
- Bleeding or bruising more easily than normal
- Feeling very tired

- Severe allergic reactions and severe skin reactions can happen with POMALYST and may cause death.
  Call your healthcare provider if you develop any of the following signs or symptoms during treatment with POMALYST:

- a red, itchy, skin rash

- peeling of your skin or blisters

- severe itching
- fever

Get emergency medical help right away if you develop any of the following signs or symptoms during treatment with POMALYST:

- swelling of your lips, mouth, tongue, or throat
- trouble breathing or swallowing
- raised red areas on your skin (hives)

- a very fast heartbeat
- you feel dizzy or faint

- Dizziness and confusion. See "What should I avoid while taking POMALYST?
- Nerve damage. Stop taking POMALYST and call your healthcare provider if you develop symptoms of nerve damage including: numbness, tingling, pain, burning sensation in your hands, legs, or feet.
- Risk of new cancers (malignancies). New cancers, including certain blood cancers (acute myelogenous leukemia or AML) have been seen in people who received POMALYST. Talk with your healthcare provider about your risk of developing new cancers if you take POMALYST.
- Tumor lysis syndrome (TLS). TLS is caused by the fast breakdown of cancer cells. TLS can cause kidney failure and the need for dialysis treatment, abnormal heart rhythm, seizure, and sometimes death. Your healthcare provider may do blood tests to check you for TLS.

Your healthcare provider may tell you to stop taking POMALYST if you develop certain serious side effects during treatment.

The most common side effects of POMALYST in people with Multiple Myeloma include:

- tiredness and weakness
- constipation
- nausea

- diarrhea
- shortness of breath
- upper respiratory tract infection

- back pain
- fever

The most common side effects of POMALYST in people with KS include:

- tiredness
- diarrhea
- abnormal kidney function tests
- decreased phosphate and calcium in the blood
- rash. See "Severe allergic reactions and severe skin reactions" above.

- nausea
- constipation
- increased blood sugar
- decreased albumin in the blood

These are not all the possible side effects of POMALYST.

Call your doctor for medical advice about side effects. You may report side effects to FDA at 1-800-FDA-1088.

How should I store POMALYST?

- Store POMALYST at room temperature between 68°F to 77°F (20°C to 25°C).
- Return any unused POMALYST to PS-Pomalidomide REMS by calling 1-888-423-5346 or your healthcare provider.

Keep POMALYST and all medicines out of the reach of children.

General information about the safe and effective use of POMALYST.

Medicines are sometimes prescribed for purposes other than those listed in a Medication Guide. Do not take POMALYST for conditions for which it was not prescribed. Do not give POMALYST to other people, even if they have the same symptoms you have. It may harm them and may cause birth defects.

If you would like more information, talk with your healthcare provider. You can ask your healthcare provider or pharmacist for information about POMALYST that is written for health professionals.

For more information, call 1-888-423-5436 or go to www.PS-PomalidomideREMS.com.

What are the ingredients in POMALYST?

Active ingredient: pomalidomide

Inactive ingredients: mannitol, pregelatinized starch, and sodium stearyl fumarate.

The 1-mg capsule shell contains gelatin, titanium dioxide, FD&C blue 2, yellow iron oxide, white ink, and black ink.
The 2-mg capsule shell contains gelatin, titanium dioxide, FD&C blue 2, yellow iron oxide, FD&C red 3, and white ink.
The 3-mg capsule shell contains gelatin, titanium dioxide, FD&C blue 2, yellow iron oxide, and white ink.
The 4-mg capsule shell contains gelatin, titanium dioxide, FD&C blue 1, FD&C blue 2, and white ink.

Marketed by: Bristol-Myers Squibb Company, Princeton, NJ 08543 USA
POMALYST® is a trademark of Celgene Corporation, a Bristol-Myers Squibb company.
POMMG.015

This Medication Guide has been approved by the U.S. Food and Drug Administration.

Revised: Feb 2025

POMALYST 1 mg Representative Packaging

NDC 59572-501-21
Pomalyst®
(pomalidomide) capsules
1 mg
WARNING: POTENTIAL FOR HUMAN BIRTH DEFECTS.
Rx only
21 Capsules
Bristol Myers Squibb

POMALYST 2 mg Representative Packaging

NDC 59572-502-21
Pomalyst®
(pomalidomide) capsules
2 mg
WARNING: POTENTIAL FOR HUMAN BIRTH DEFECTS.
Rx only
21 Capsules
Bristol Myers Squibb

POMALYST 3 mg Representative Packaging

NDC 59572-503-21
Pomalyst®
(pomalidomide) capsules
3 mg
WARNING: POTENTIAL FOR HUMAN BIRTH DEFECTS.
Rx only
21 Capsules
Bristol Myers Squibb

POMALYST 4 mg Representative Packaging

NDC 59572-504-21
Pomalyst®
(pomalidomide) capsules
4 mg
WARNING: POTENTIAL FOR HUMAN BIRTH DEFECTS.
Rx only
21 Capsules
Bristol Myers Squibb